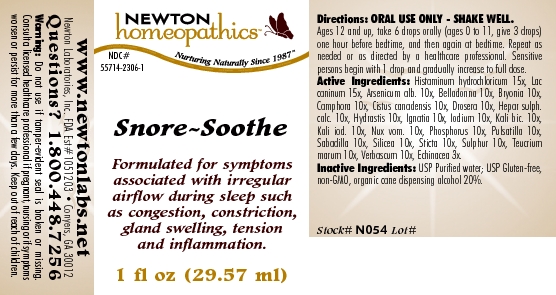 DRUG LABEL: Snore Soothe 
NDC: 55714-2306 | Form: LIQUID
Manufacturer: Newton Laboratories, Inc.
Category: homeopathic | Type: HUMAN OTC DRUG LABEL
Date: 20110301

ACTIVE INGREDIENTS: Histamine Dihydrochloride 15 [hp_X]/1 mL; Canis Lupus Familiaris Milk 15 [hp_X]/1 mL; Arsenic Trioxide 10 [hp_X]/1 mL; Atropa Belladonna 10 [hp_X]/1 mL; Bryonia Alba Root 10 [hp_X]/1 mL; Camphor (natural) 10 [hp_X]/1 mL; Helianthemum Canadense 10 [hp_X]/1 mL; Drosera Rotundifolia Flowering Top 10 [hp_X]/1 mL; Calcium Sulfide 10 [hp_X]/1 mL; Goldenseal 10 [hp_X]/1 mL; Strychnos Ignatii Seed 10 [hp_X]/1 mL; Iodine 10 [hp_X]/1 mL; Potassium Dichromate 10 [hp_X]/1 mL; Potassium Iodide 10 [hp_X]/1 mL; Strychnos Nux-vomica Seed 10 [hp_X]/1 mL; Phosphorus 10 [hp_X]/1 mL; Pulsatilla Vulgaris 10 [hp_X]/1 mL; Schoenocaulon Officinale Seed 10 [hp_X]/1 mL; Silicon Dioxide 10 [hp_X]/1 mL; Lobaria Pulmonaria 10 [hp_X]/1 mL; Sulfur 10 [hp_X]/1 mL; Teucrium Marum 10 [hp_X]/1 mL; Verbascum Thapsus 10 [hp_X]/1 mL; Echinacea, Unspecified 3 [hp_X]/1 mL
INACTIVE INGREDIENTS: Alcohol

Snore - Soothe

INDICATIONS & USAGE SECTION

Snore - Soothe Formulated for symptoms associated with irregular airflow during sleep such as congestion, constriction, gland swelling, tension and inflammation.

DOSAGE & ADMINISTRATION SECTION

ORAL USE ONLY - SHAKE WELL. Ages 12 and up, take 6 drops orally (ages 0 to 11, give 3 drops) one hour before bedtime, and then again at bedtime. Repeat as needed or as directed by a healthcare professional. Sensitive persons begin with 1 drop and gradually increase to full dose.

OTC - ACTIVE INGREDIENT SECTION

Histaminum hydrochloricum 15x, Lac caninum 15x, Arsenicum alb. 10x, Belladonna 10x, Bryonia 10x, Camphora 10x, Cistus canadensis 10x, Drosera 10x, Hepar sulph.calc. 10x, Hydrastis 10x, Ignatia 10x, Iodium 10x, Kali bic. 10x, Kali iod. 10x, Nux vom. 10x, Phosphorus 10x, Pulsatilla 10x, Sabadilla 10x, Silicea 10x, Sticta 10x, Sulphur 10x, Teucrium marum 10x, Verbascum 10x, Echinacea 3x.

OTC - PURPOSE SECTION

Formulated for symptoms associated with irregular airflow during sleep such as congestion, constriction, gland swelling, tension and inflammation.

INACTIVE INGREDIENT SECTION

Inactive Ingredients: USP Purified Water; USP Gluten-free, non-GMO, organic cane dispensing alcohol 20%.

QUESTIONS SECTION

www.newtonlabs.net Newton Laboratories, Inc. FDA Est # 1051203 - Conyers, GA 30012
Questions? 1.800.448.7256

WARNINGS SECTION

Warning: Do not use if tamper - evident seal is broken or missing. Consult a licensed healthcare professional if pregnant, nursing or if symptoms worsen or persist for more than a few days. Keep out of reach of children.

OTC - PREGNANCY OR BREAST FEEDING SECTION

Consult a licensed healthcare professional if pregnant, nursing or if symptoms worsen or persist for more than a few days.

OTC - KEEP OUT OF REACH OF CHILDREN SECTION

Keep out of reach of children.